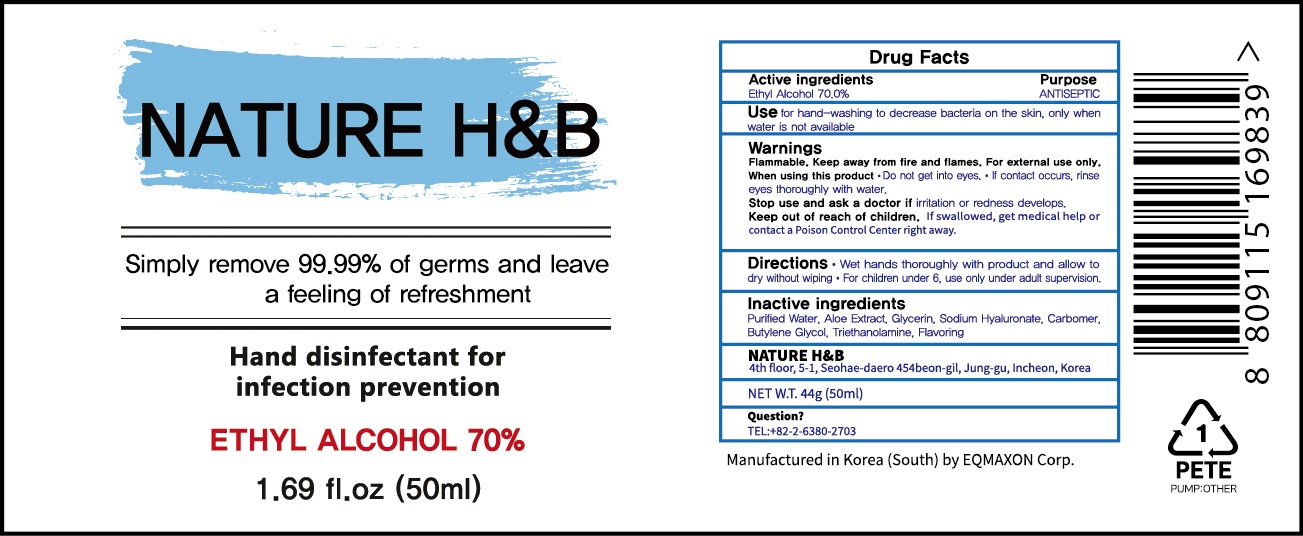 DRUG LABEL: NATURE HNB Hand Sanitizer
NDC: 55526-0013 | Form: SPRAY
Manufacturer: EQMAXON Corp
Category: otc | Type: HUMAN OTC DRUG LABEL
Date: 20200521

ACTIVE INGREDIENTS: ALCOHOL 35 mL/50 mL
INACTIVE INGREDIENTS: Water; ALOE; Glycerin; HYALURONATE SODIUM; CARBOMER HOMOPOLYMER, UNSPECIFIED TYPE; Butylene Glycol; TROLAMINE

ACTIVE INGREDIENT

Ethyl Alcohol 70.0%

INACTIVE INGREDIENT

Purified Water, Aloe Extract, Glycerin, Sodium Hyaluronate, Carbomer, Butylene Glycol, Triethanolamine, Flavoring

PURPOSE

Purpose: ANTISEPTIC

WARNINGS

Flammable. Keep away from fire and flames. For external use only.

When using this product • Do not get into eyes. • If contact occurs, rinse eyes thoroughly with water.

Stop use and ask a doctor if irritation or redness develops.

Keep out of reach of children. If swallowed, get medical help or contact a Poison Control Center right away

KEEP OUT OF REACH OF CHILDREN

If swallowed, get medical help or contact a Poison Control Center right away

Uses

for hand-washing to decrease bacteria on the skin, only when water is not available

Directions

Wet hands thoroughly with product and allow to dry without wiping

For children under 6, use only under adult supervision.

Questions?

+82-2-6380-2703